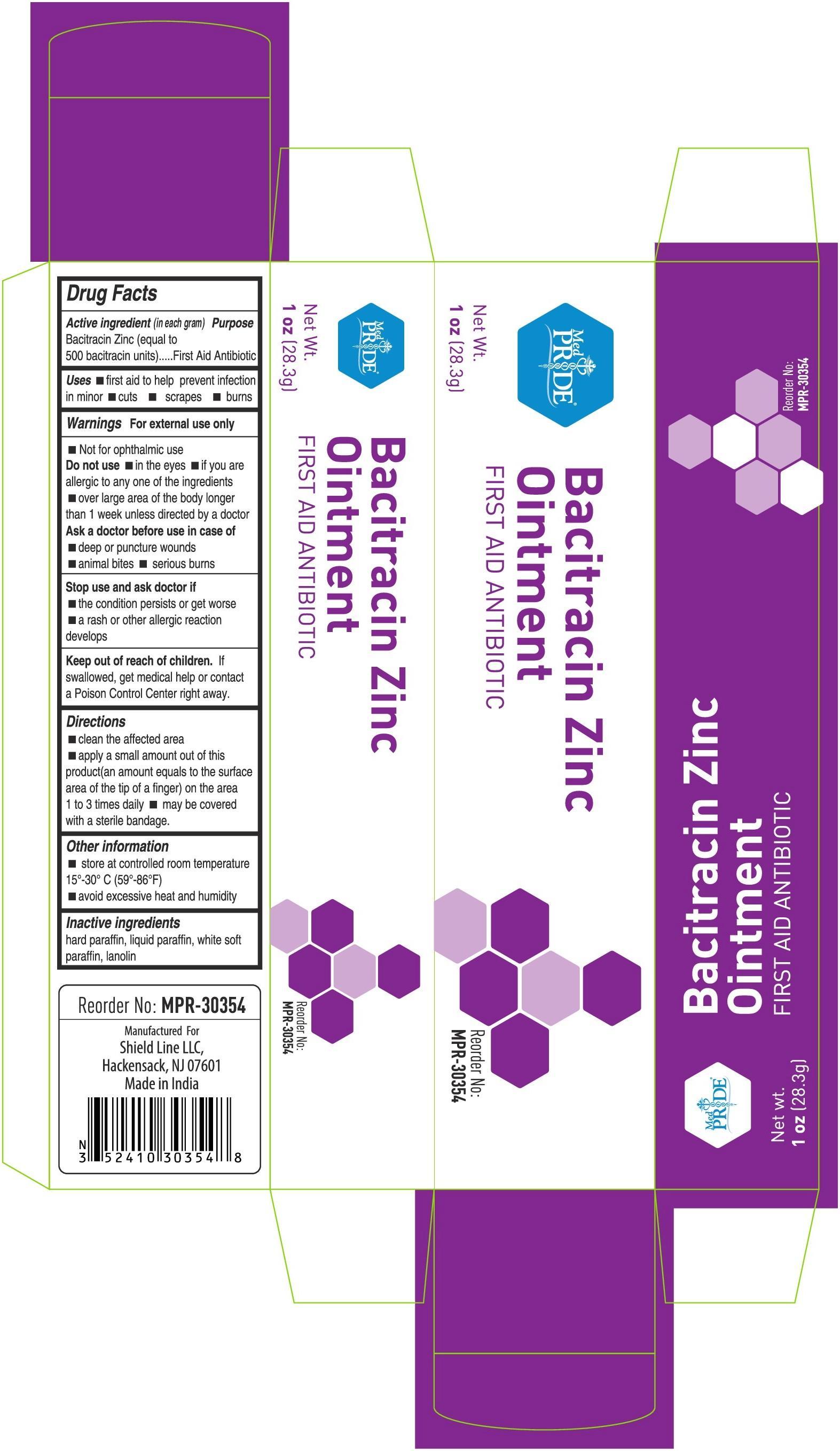 DRUG LABEL: Medpride
NDC: 52410-3035 | Form: OINTMENT
Manufacturer: Shield Line LLC
Category: otc | Type: HUMAN OTC DRUG LABEL
Date: 20250815

ACTIVE INGREDIENTS: BACITRACIN ZINC 500 [USP'U]/1 g
INACTIVE INGREDIENTS: MINERAL OIL; PETROLATUM; LANOLIN; PARAFFIN

Medpride Bacitracin Zinc

Active Ingredient (in each gram)

Bacitracin Zinc (equal to 500 bacitracin units)

Purpose

First Aid Antibiotic

Uses

■ first aid to help prevent infection in minor ■ cuts ■ scrapes ■ burns

Warnings

For external use only

Do not use

■ Not for opthalmic use Do not use ■ in the eyes ■ if you are allergic to any of the ingredients ■ over large areas of the body longer than 1 week unless directed by a doctor

Ask a doctor before use in case of

■ deep or puncture wounds

■ animal bites ■ serious burns

Stop use and ask a doctor if

■ the condition persists or gets worse

■ a rash or other allergic reaction develops

Keep out of reach of children. If swallowed, get medical help or contact a Poison Control Center right away.

Directions

■ clean the affected area

■ apply a small amount of this product (an amount equal to the surface area of the tip of a finger) on the area 1 to 3 times daily •may be covered with a sterile bandage

Other Information

■ store at room temperature 15-30C (59-86F)

■ avoid excessive heat and humidity

Inactive Ingredients

hard paraffin, liquid paraffin, white soft paraffin, lanolin